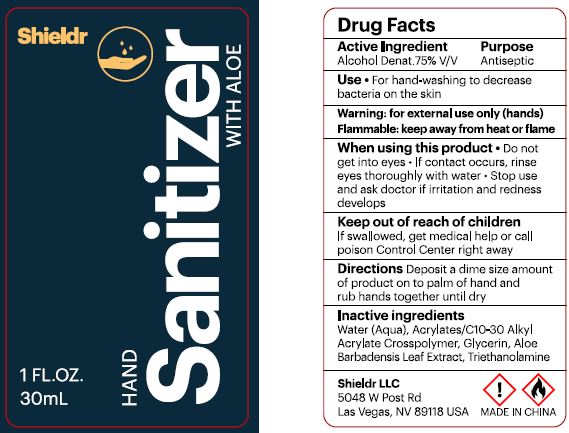 DRUG LABEL: HAND SANITIZER
NDC: 76854-101 | Form: SOLUTION
Manufacturer: Fujian Shuangfei Daily Chemicals Co.,Ltd.
Category: otc | Type: HUMAN OTC DRUG LABEL
Date: 20200723

ACTIVE INGREDIENTS: ALCOHOL 75 mL/100 mL
INACTIVE INGREDIENTS: WATER; CARBOMER INTERPOLYMER TYPE A (ALLYL SUCROSE CROSSLINKED); GLYCERIN; ALOE VERA LEAF; TROLAMINE

SHIELDR HAND SANITIZER WITH ALOE - 75% V/V ALCOHOL DENAT

ACTIVE INGREDIENT

ALCOHOL DENAT. 75% V/V

PURPOSE

ANTISEPTIC

USES

FOR HAND-WASHING TO DECREASE BACTERIA ON THE SKIN

WARNINGS

For external use only: hands

Flammable. Keep away from heat or flame.

When using this product

- Do not get into eyes. If contact occurs, rinse eyes thoroughly with water.
- Stop use and ask a doctor if irritation and redness develops

Keep out of reach of children.

If swallowed, get medical help or call Poison Control Center right away.

DIRECTIONS

Deposit a dime size amount of product on to palm of hand and rub hands together until dry.

INACTIVE INGREDIENTS

Water (Aqua), Acrylates/C10-30 Alkyl Acrylate Crosspolymer, Glycerin, Aloe Barbadensis Leaf Extract, Triethanolamine